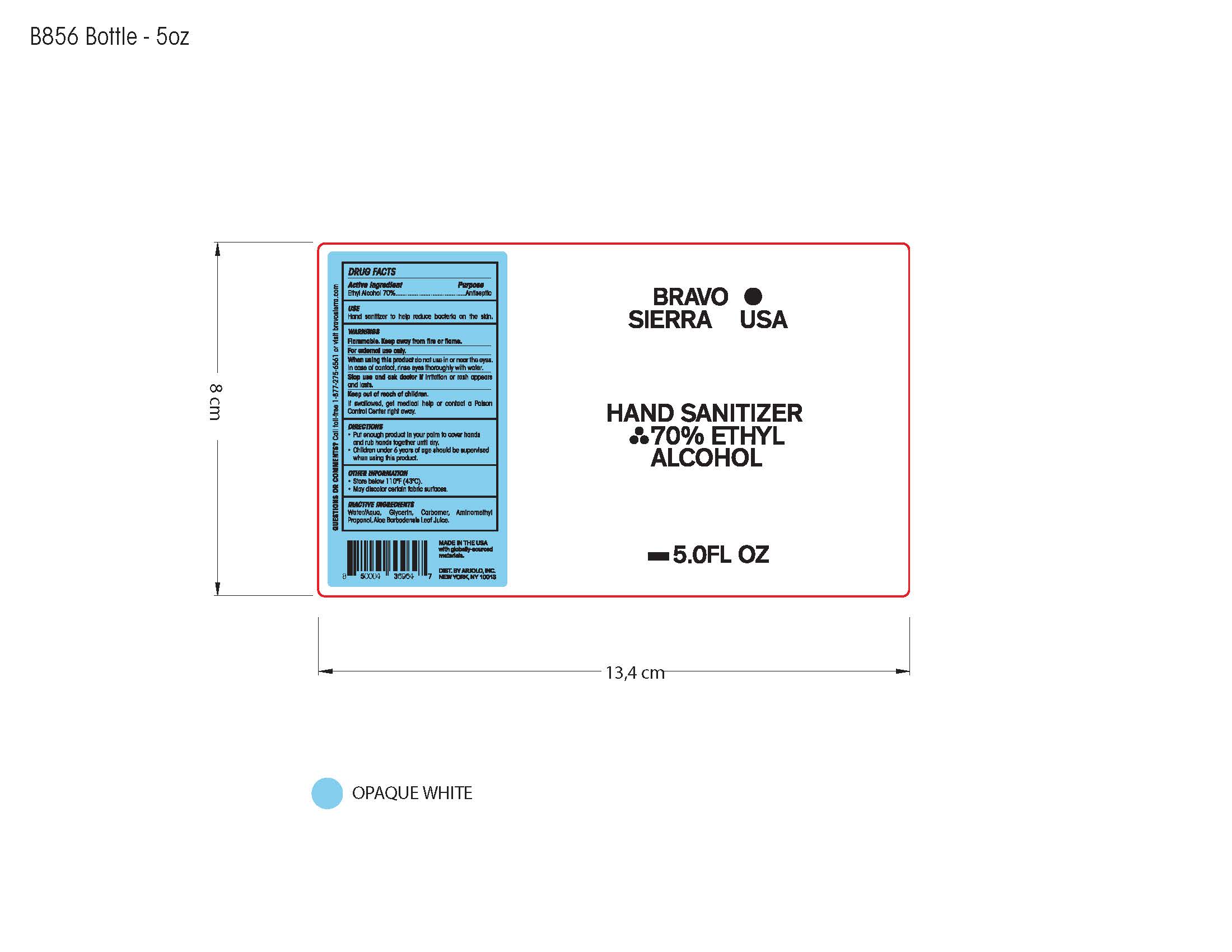 DRUG LABEL: Bravo Sierra USA Hand Sanitizer 70% Ethyl Alcohol
NDC: 73206-030 | Form: SOLUTION
Manufacturer: ARJOLO, INC.
Category: otc | Type: HUMAN OTC DRUG LABEL
Date: 20200714

ACTIVE INGREDIENTS: ALCOHOL 70 mL/100 mL
INACTIVE INGREDIENTS: GLYCERIN; CARBOMER 940; WATER; ALOE VERA LEAF; AMINOMETHYL PROPANEDIOL

DRUG FACTS

Active Ingredient(s)

Ethyl Alcohol 70%

Purpose

Antiseptic

Use

• Hand sanitizer to help reduce bacteria on the skin

Warnings

For external use only. Flammable. Keep away from heat or flame

Do not use

- in children less than 2 months of age
- on open skin wounds

When using this product do not use in or near the eyes. In case of contact, rinse eyes thoroughly with water.

Stop Use and ask doctor if irritation or rash appears and lasts

Keep out of reach of children. If swallowed, get medical help or contact a Poison Control Center right away.

Directions

- Put enough product in your palm to cover hands and rub hands together until dry. • Children under 6 years of age should be supervised when using this product.

Other information

- Store below 110ºF • May discolor certain fabric surfaces.

Inactive ingredients

Water/Aqua, Glycerin, Carbomer, Aminomethyl Propanol, Aloe Barbadensis Leaf Juice.